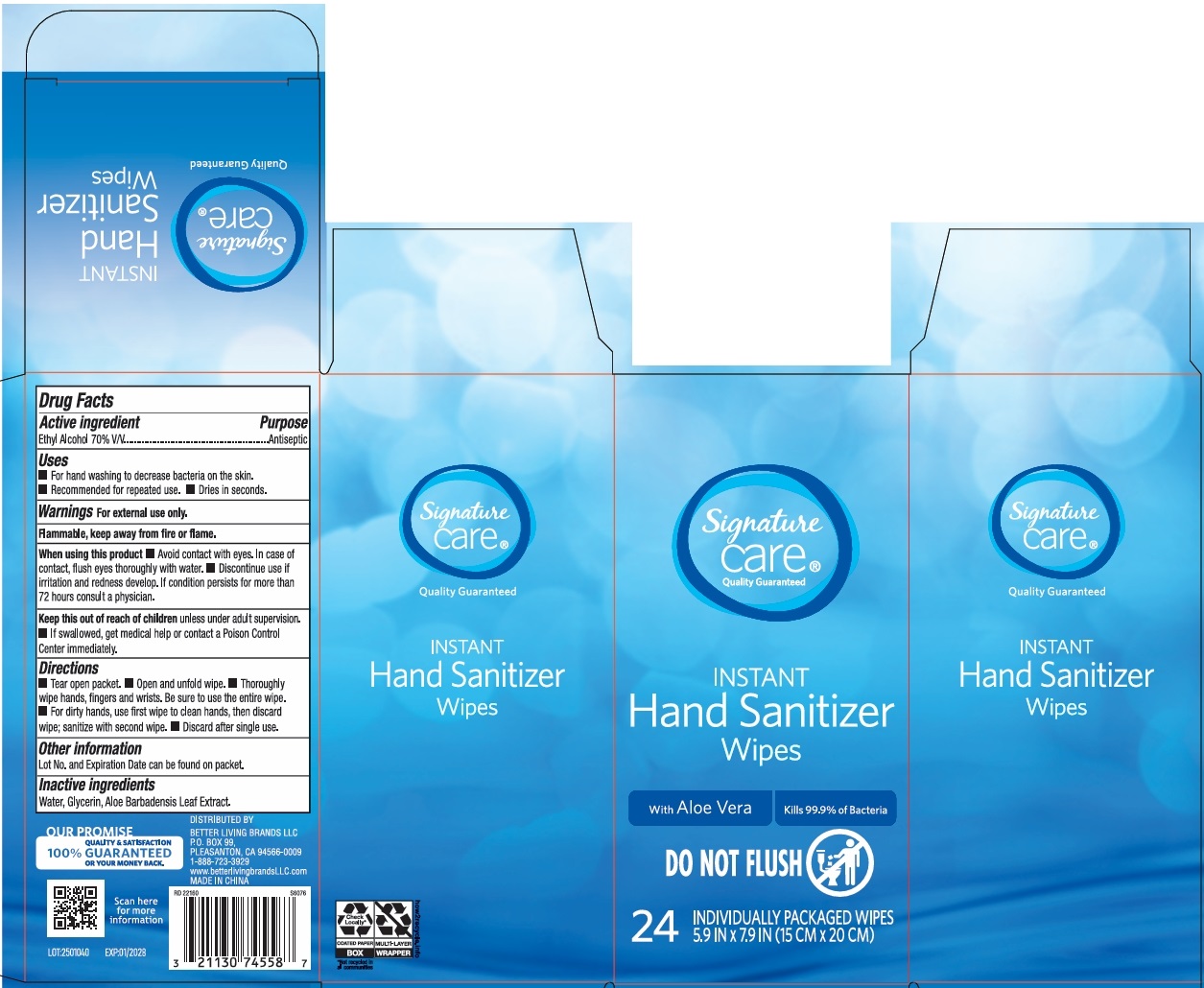 DRUG LABEL: Signature Care Instant Hand Sanitizer Wipes
NDC: 74149-113 | Form: SWAB
Manufacturer: Yiwu Yangjie Daily Chemicals Co.,Ltd.
Category: otc | Type: HUMAN OTC DRUG LABEL
Date: 20250516

ACTIVE INGREDIENTS: ALCOHOL 70 g/100 g
INACTIVE INGREDIENTS: WATER; GLYCERIN; ALOE BARBADENSIS LEAF JUICE

Ethyl Alcohol Wipes

Active Ingredient

Ethyl Alcohol 70% v/v

Purpose

Antiseptic

USE

- For hand washing to decrease bacteria on the skin.
- Recommended for repeated use.
- Dries in seconds.

Warning

- For external use only.
- Flammable, keep away from fire or flame.

When using this product

- Avoid contact with eyes. In case of contact, flush eyes thoroughly with water.
- Discontinue use if irritation and redness develop. If condition persists for more than 72 hours conslt a physician.

Other Information:

- Lot no. and Expiration date can be found on packet

KEEP OUT OF REACH OF CHILDREN

●If swallowed, get medical help or contact a Poison Contrl Center immediately.

Directions

- tear open packet.
- open and unfold wipe.
- thoroughly wipe hands, fingers and wrists. Be sure to use the entire wipe.
- for dirty hands, use first wipe to clean hands, then discard wipe; sanitize with second wipe.
- discard after single use.

Inactive ingredients

water, glycerin, alow barbadensis leaf extract.